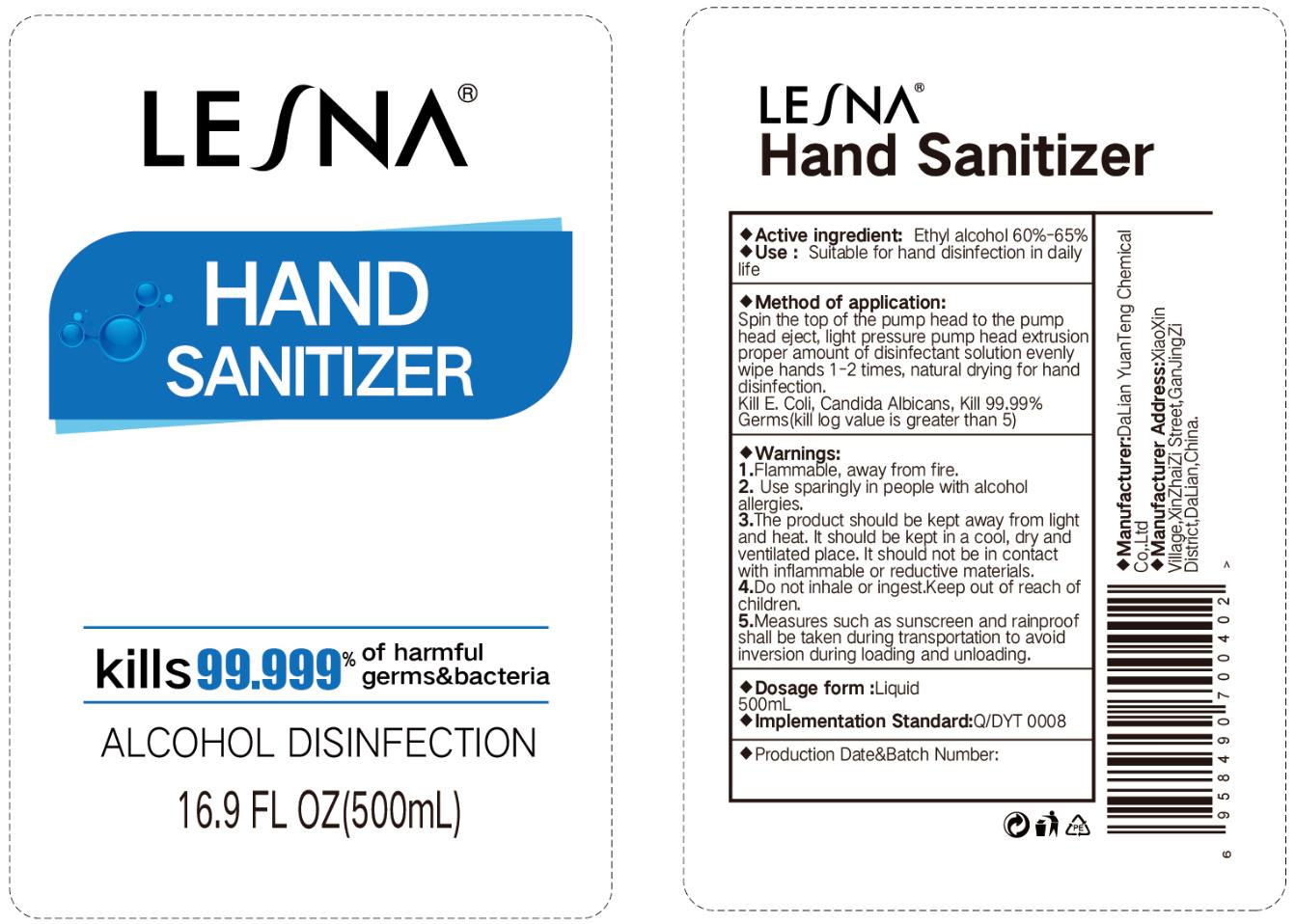 DRUG LABEL: LESNA Hand Sanitizer
NDC: 74405-1005 | Form: LIQUID
Manufacturer: Dalian Yuanteng Chemical Co., Ltd
Category: otc | Type: HUMAN OTC DRUG LABEL
Date: 20200410

ACTIVE INGREDIENTS: ALCOHOL 300 mL/500 mL
INACTIVE INGREDIENTS: TROLAMINE 1.75 mL/500 mL; GLYCERIN 30 mL/500 mL; WATER 166.5 mL/500 mL; CARBOMER 940 1.75 mL/500 mL

YuanTeng, Hand Sanitizer, Gel, 60% Ethanol, 500mL

Active Ingredient(s)

Ethanol 60% v/v. Purpose: Antiseptic

Purpose

Antiseptic, Hand Sanitizer

Use

Hand Sanitizer to help reduce bacteria that potentially can cause disease. For use when soap and water are not available.

Warnings

Flammable. For external use only. Keep away from heat or flame.

Do not use

- on children less than 2 months of age
- on open skin wounds

When using this product keep out of eyes, ears, and mouth.

In case of contact with eyes, rinse eyes thoroughly with water.

Stop use and ask a doctor if irritation or rash occurs. These may be signs of a serious condition.

Keep out of reach of children. If swallowed, get medical help or contact a Poison Control Center right away.

Directions

- Place enough product on hands to cover all surfaces. Rub hands together until dry.
- Supervise children under 6 years of age when using this product to avoid swallowing.

Other information

- Store between 59-86℉ (15-30℃)
- Avoid freezing and excessive heat above 104℉ (40℃)

Inactive ingredients

Water, Glycerol, Carbomer 940, Trolamine765